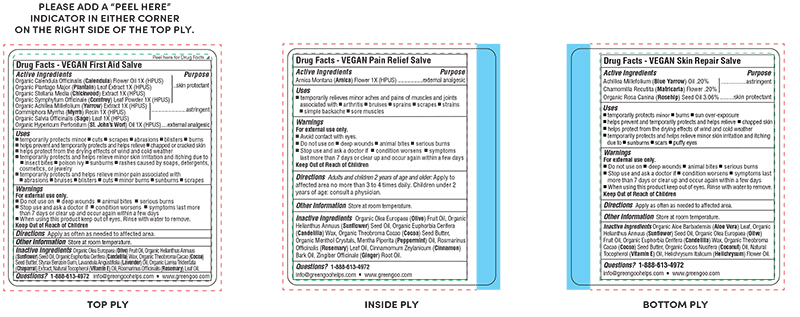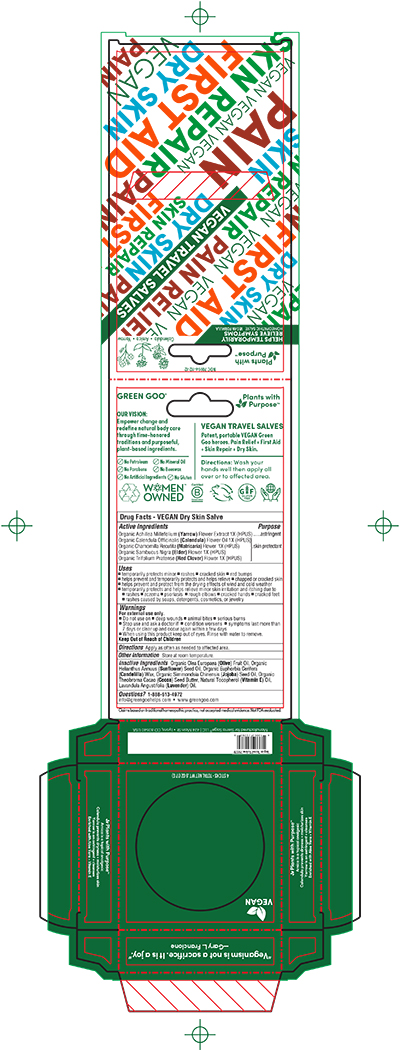 DRUG LABEL: Everyday Essential Travel Salves 4pc Kit
NDC: 70994-112 | Form: KIT | Route: TOPICAL
Manufacturer: Sierra Sage Herbs LLC
Category: homeopathic | Type: HUMAN OTC DRUG LABEL
Date: 20220310

ACTIVE INGREDIENTS: ROSA MOSCHATA OIL 1 [hp_X]/100 g; ACHILLEA MILLEFOLIUM 1 [hp_X]/100 g; MATRICARIA RECUTITA 1 [hp_X]/100 g; TRIFOLIUM PRATENSE FLOWER 1 [hp_X]/100 g; CHAMOMILE 1 [hp_X]/100 g; ACHILLEA MILLEFOLIUM 1 [hp_X]/100 g; CALENDULA OFFICINALIS FLOWER 1 [hp_X]/100 g; SAMBUCUS NIGRA FLOWER 1 [hp_X]/100 g; STELLARIA MEDIA 1 [hp_X]/100 g; ACHILLEA MILLEFOLIUM FLOWER 1 [hp_X]/100 g; SALVIA OFFICINALIS WHOLE 1 [hp_X]/100 g; COMFREY LEAF 1 [hp_X]/100 g; ST. JOHN'S WORT 1 [hp_X]/100 g; CALENDULA OFFICINALIS FLOWER 1 [hp_X]/100 g; COMMIPHORA MYRRHA WHOLE 1 [hp_X]/100 g; PLANTAGO MAJOR 1 [hp_X]/100 g; ARNICA MONTANA FLOWER 1 [hp_X]/100 g
INACTIVE INGREDIENTS: HELICHRYSUM ITALICUM FLOWER OIL; COCONUT OIL; ALPHA-TOCOPHEROL; ALOE VERA LEAF; OLIVE OIL; THEOBROMA CACAO WHOLE; SUNFLOWER OIL; CANDELILLA WAX; LAVENDER OIL; OLIVE OIL; JOJOBA OIL; SUNFLOWER OIL; CANDELILLA WAX; THEOBROMA CACAO WHOLE; ALPHA-TOCOPHEROL; OLIVE OIL; .ALPHA.-TOCOPHEROL; SUNFLOWER OIL; CANDELILLA WAX; LARREA TRIDENTATA LEAF; STYRAX BENZOIN RESIN; THEOBROMA CACAO WHOLE; ROSEMARY OIL; LAVENDER OIL; CINNAMON OIL; MENTHOL; MENTHA PIPERITA; SUNFLOWER OIL; CANDELILLA WAX; THEOBROMA CACAO WHOLE; GINGER OIL; ROSEMARY OIL; OLIVE OIL

Everyday Essential Travel Salves 4pc Kit

Purpose Section

Skin Protectant

Astringent

External Analgesic

Active Ingredients Section

Organic Calendula Officinalis (Calendula) Flower Oil 1X (HPUS)

Organic Plantago Major (Plantain) Leaf Extract 1X (HPUS)

Organic Stellaria Media (Chickweed) Extract 1X (HPUS)

Organic Symphytum Officinale (Comfrey) Leaf Powder 1X (HPUS)

OrganicAchilleaMillefolium(Yarrow)Extract1X(HPUS)

Commiphora Myrrha (Myrrh) Resin 1X (HPUS)

Organic Salvia Officinalis (Sage) Leaf 1X (HPUS)

Organic Hypericum Perforatum (St. John’s Wort) Oil 1X (HPUS)

Indications & Usage

• temporarily protects minor • cuts • scrapes • abrasions • bruises • blisters • burns

▪ temporarily protects and helps relieve • chapped or cracked skin

▪ helps protect from the drying effects of wind and cold weather

▪ temporarily protects and helps relieve minor skin irritations and itching due to • insect bites • poison ivy • sunburns

• rashes caused by soaps, detergents, cosmetics, or jewelry

▪ temporarily protects and helps relieves minor pain associated with • abrasions • bruises • blisters • cuts • minor burns • sunburns

• scrapes

Keep out of Reach of Children

Warnings Section

Warnings

For external use only.

• Do not use on • deep wounds • animal bites • serious burns

• Stop use and ask a doctor if • condition worsens • symptoms last more than 7 days or clear up and occur again within a few days

• When using this product keep out of eyes. Rinse with water to remove.

Storage & Handling Section

Store at room temperature.

Dosage & Administration Section

Apply as often as needed to affected area.

Inactive Ingredients Section

Organic Olea Europaea (Olive) Fruit Oil, Organic Helianthus Annuus (Sunflower) Seed Oil, Organic Euphorbia Cerifera (Candelilla) Wax, Organic Theobroma Cacao (Cocoa) Seed Butter, Styrax Benzoin Gum, Lavandula Angustifolia (Lavender) Oil, Organic Larrea Tridentata (Chaparral) Extract, Tocopherol (Vitamin E), Rosmarinus Officinalis (Rosemary) Leaf Oil.